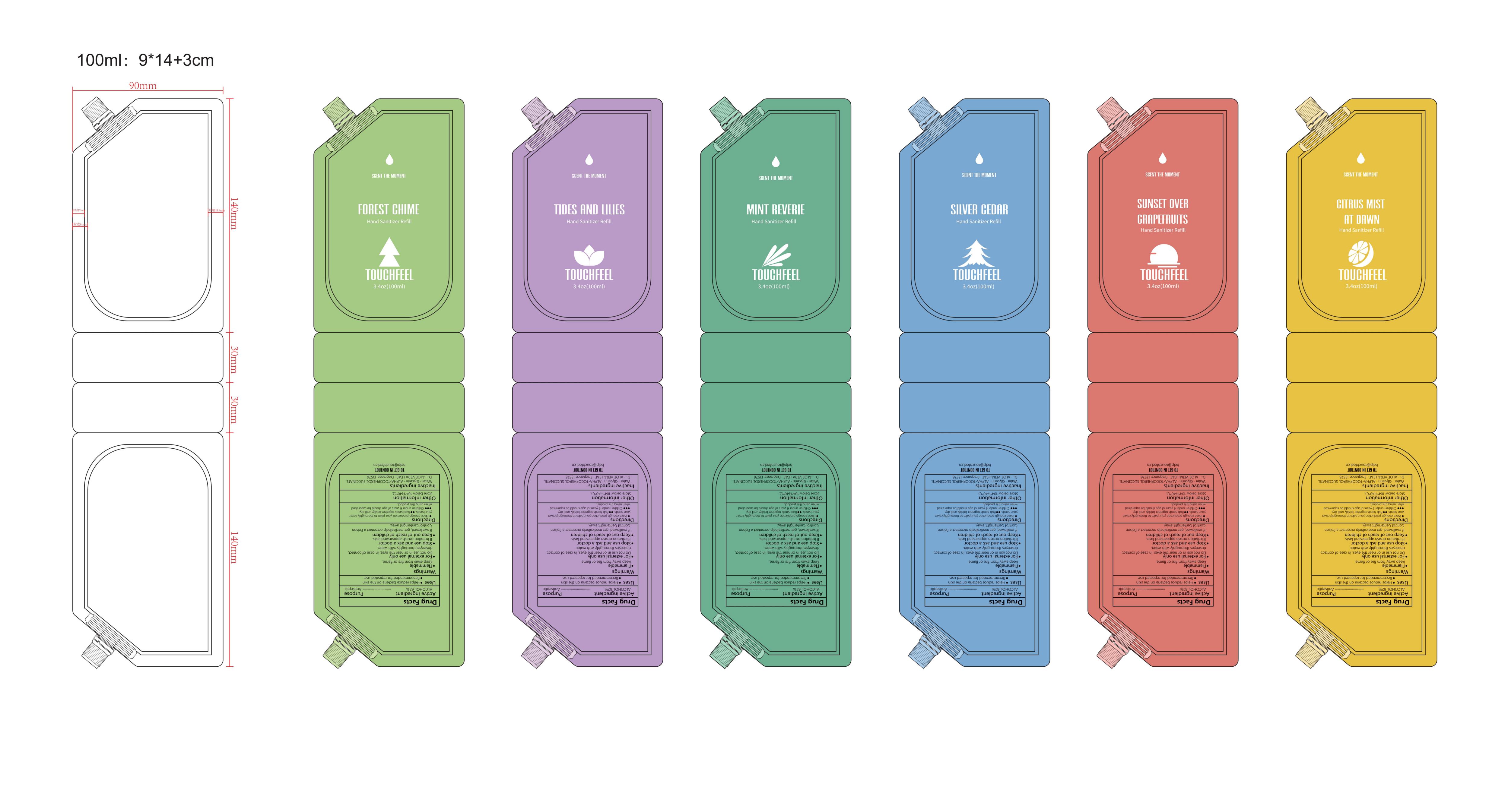 DRUG LABEL: Hand Sanitizer Refill
NDC: 84778-098 | Form: LOTION
Manufacturer: Guangzhou Yixin Cross-border E-commerce Co., Ltd.
Category: otc | Type: HUMAN OTC DRUG LABEL
Date: 20251015

ACTIVE INGREDIENTS: ALCOHOL 62 mL/100 mL
INACTIVE INGREDIENTS: WATER; ALOE VERA LEAF; FRAGRANCE 13576; GLYCERIN; .ALPHA.-TOCOPHEROL SUCCINATE, D-

Active ingredients

ALCOHOL 62%

Purpose

Antiseptic

Uses

Use hand sanitizer to help reduce disease - causing bacteria on the skin. For use when soap and water are not available.

Warnings

Flammable. Keep away from fire, flame, or extreme heat. For external use only.

Dosage and administration

Apply liberally to hands and rub thoroughly until dry. Supervise children in the use of this product. Use as often as needed.

Do not use in children less than 2 months of age on open skin wounds.

When using section

Avoid contact with eyes, ears, and mouth. In case of contact with eyes, rinse eyes thoroughly with water. Avoid contact with broken skin.

stop use

Stop use and ask a doctor if irritation, redness or rash develops. These may be signs of a serious condition.

Keep out of reach of children. If swallowed, get medical help or contact a poison control center right away.

Inactive ingredients

Water·Glycerin.ALPHA.-TOCOPHEROL SUCCINATE, D-·ALOE VERA LEAF·Fragrance 13576